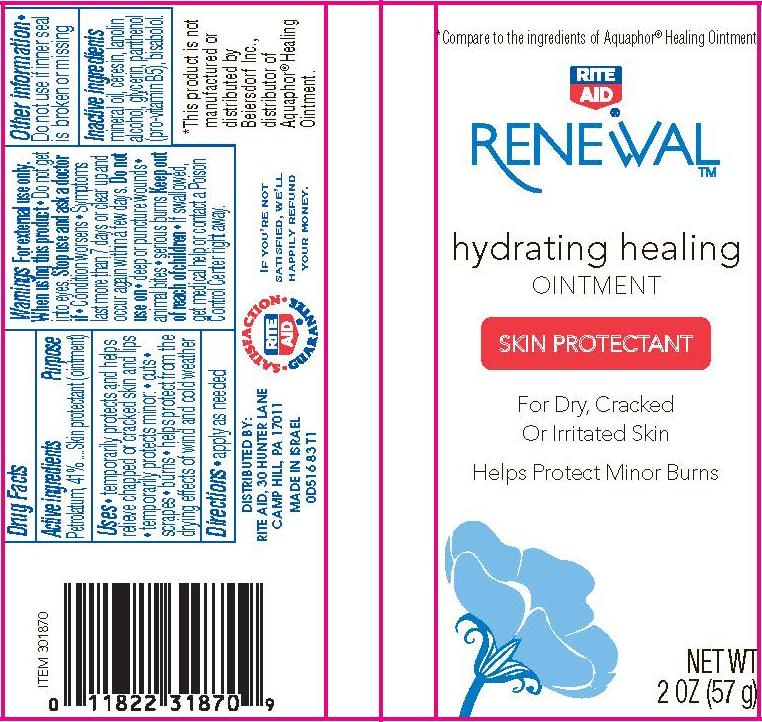 DRUG LABEL: Renewal Hydrating Healing
NDC: 11822-5161 | Form: OINTMENT
Manufacturer: Rite Aid
Category: otc | Type: HUMAN OTC DRUG LABEL
Date: 20130911

ACTIVE INGREDIENTS: PETROLATUM 41 g/100 g
INACTIVE INGREDIENTS: MINERAL OIL; CERESIN; LANOLIN; ALCOHOL; GLYCERIN; PANTHENOL; LEVOMENOL

RenewalTM hydrating healing ointment

Active ingredient

Petrolatum........41.0%

Purpose

Skin Protectant (ointment)

Uses

- temporarily protects and helps relieve chapped or cracked skin and lips
- temporarily protects minor: cuts, scrapes, burns
- helps protect from the drying effects of wind and cold weather

Warnings

For external use only.

When using this product

- do not get into eyes

Stop use and ask a doctor if

- condition worsens
- symptoms last more than 7 days or clear up and occur again within a few days

Do not use on

- deep or puncture wounds, animal bites, serious burns

Keep Out of Reach of Children.

If swallowed, get medical help or contact a Poison Control Center right away.

Directions

- apply as needed

Other Information

- do not use if inner seal is broken or missing

Inactive ingredients

mineral oil, ceresin, lanolin, alcohol, glycerin, panthenol (pro-vitamin B5), bisabolol

Package/Label Principal Display Panel

RenewalTM hydrating healing ointment

Skin Protectant

For Dry, Cracked or Irritated Skin

Helps Protect Minor Burns

NET WT. 2 OZ. (57 g)

*Compare to the ingredients of Aquaphor® Healing Ointment

DISTRIBUTED BY:
RITE AID, 30 HUNTER LANE
CAMP HILL, PA 17011
www.meijer.com

MADE IN ISRAEL

0D516 83 T1

*This product is not manufactured or distributed by Beiersdorf Inc., distributor of Aquaphor® Healing Ointment

Carton Label